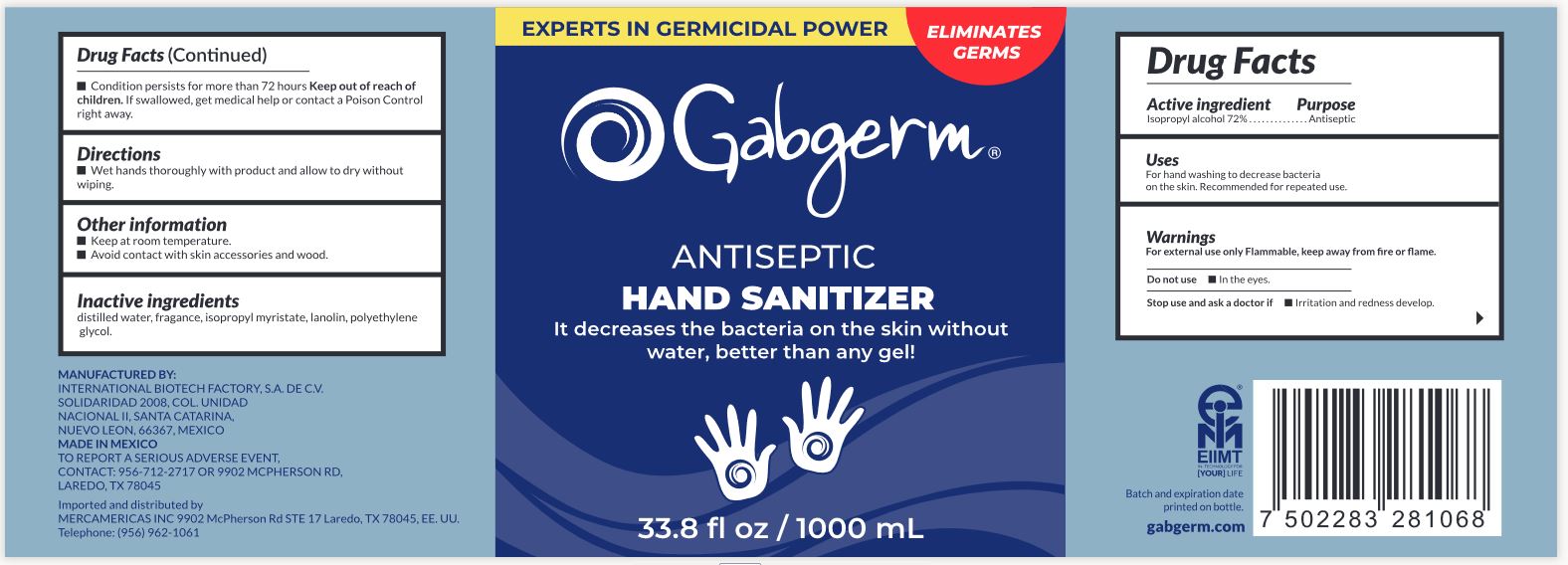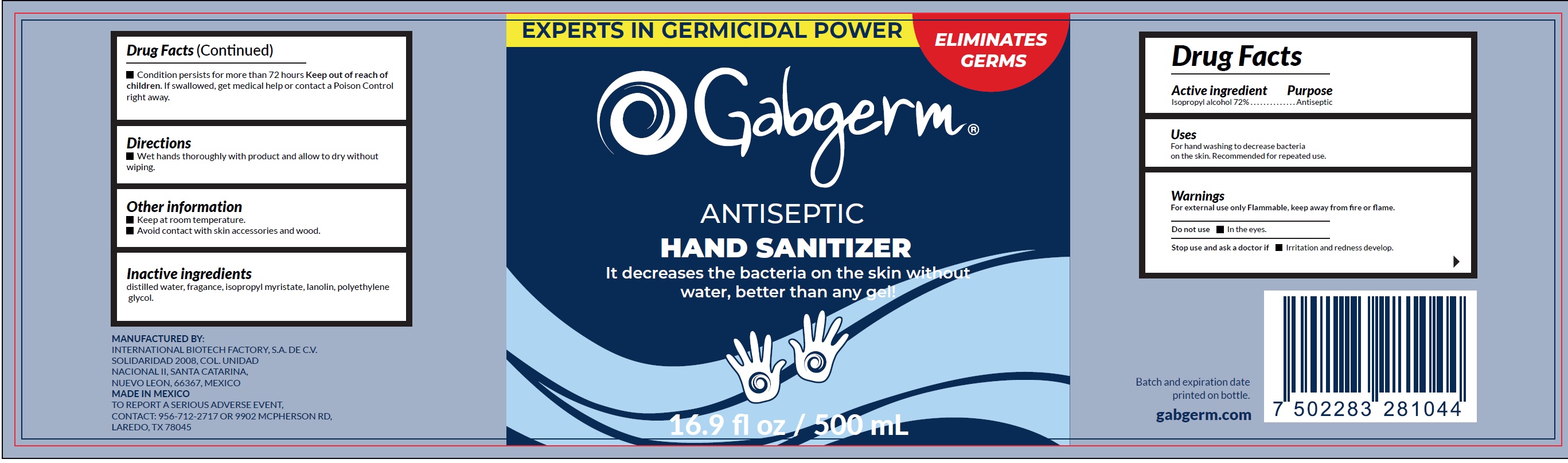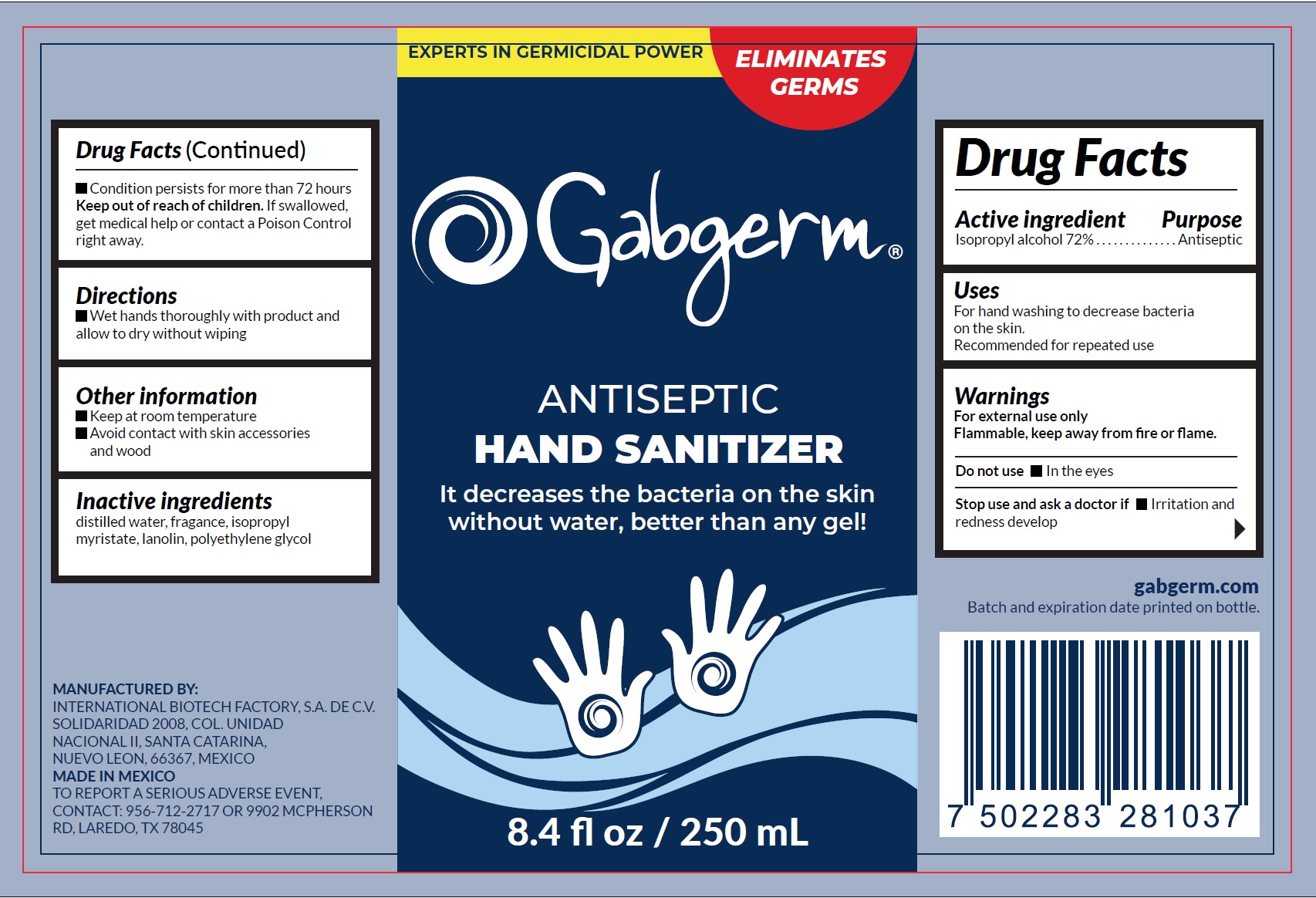 DRUG LABEL: Gabgerm Antisec hand sanitizer
NDC: 80284-002 | Form: LIQUID
Manufacturer: International Biotech Factory, S.A. de C.V.
Category: otc | Type: HUMAN OTC DRUG LABEL
Date: 20231221

ACTIVE INGREDIENTS: ISOPROPYL ALCOHOL 72 mL/100 mL
INACTIVE INGREDIENTS: WATER; ISOPROPYL MYRISTATE; LANOLIN; POLYETHYLENE GLYCOL, UNSPECIFIED

Gabgerm Antisec hand sanitizer

Active ingredient

Isopropyl alcohol 72%

Purpose

Antiseptic

Uses

For hand washing to decrease bacteria on the skin. Recommended for repeated use.

Warnings

For external use only Flammable, keep away from fire or flame.

Do not use

- In the eyes.

Stop use and ask a doctor if

- Irritation and redness develop.
- Condition persists for more than 72 hours

Keep out of reach of children.

If swallowed, get medical help or contact a Poison Control right away.

Directions

- Wet hands thoroughly with product and allow to dry without wiping.

Other information

- Keep at room temperature.
- Avoid contact with skin accessories and wood.

Inactive ingredients

distilled water, fragance, isopropyl myristate, lanolin, polyethylene glycol.